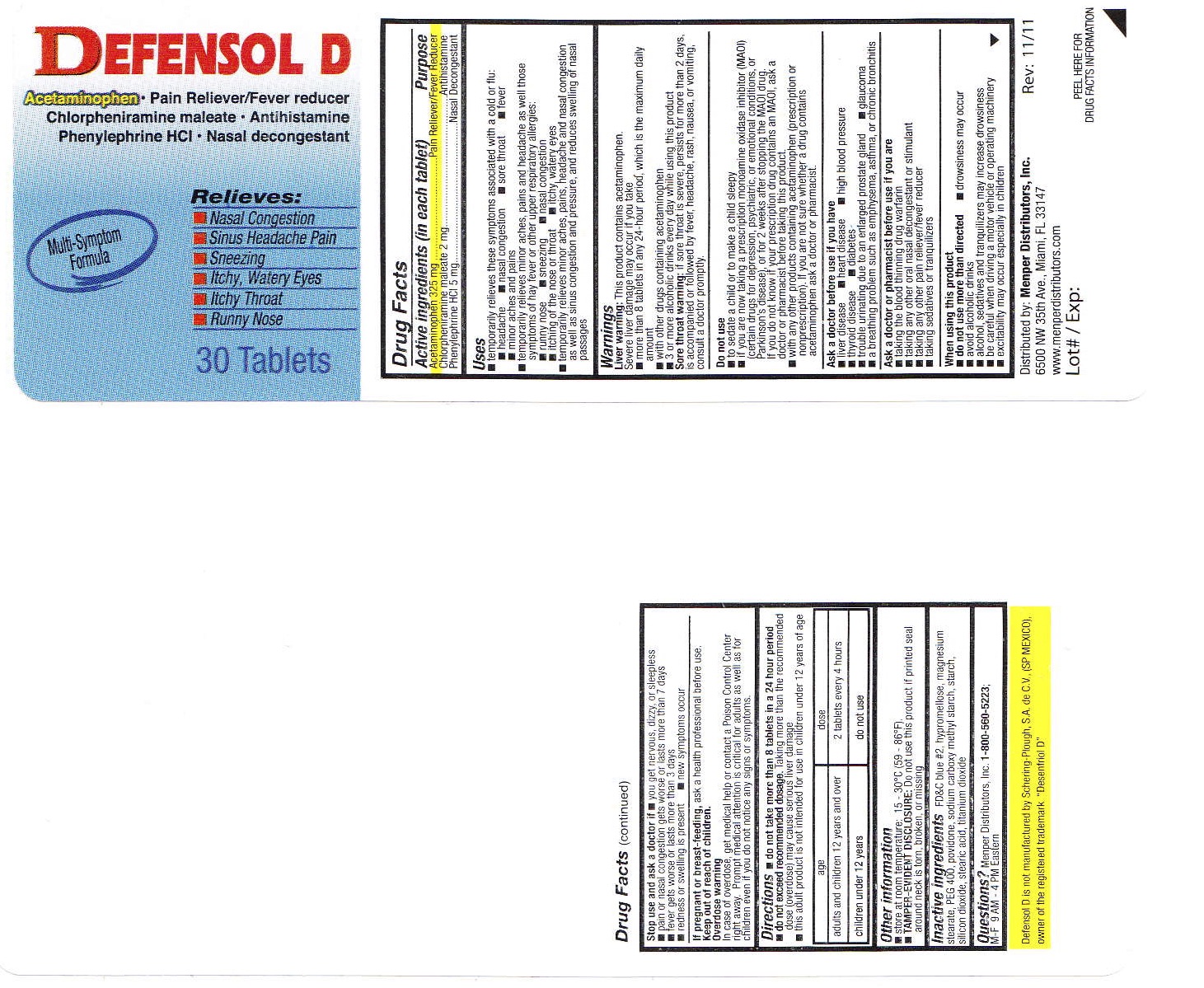 DRUG LABEL: Defensol D
NDC: 53145-005 | Form: TABLET
Manufacturer: Menper Distributors, Inc.
Category: otc | Type: HUMAN OTC DRUG LABEL
Date: 20250722

ACTIVE INGREDIENTS: ACETAMINOPHEN 325 mg/1 1; CHLORPHENIRAMINE MALEATE 2 mg/1 1; PHENYLEPHRINE HYDROCHLORIDE 5 mg/1 1
INACTIVE INGREDIENTS: FD&C BLUE NO. 2; HYPROMELLOSE 2208 (100 MPA.S); MAGNESIUM STEARATE; POLYETHYLENE GLYCOL 400; POVIDONE; STARCH, PREGELATINIZED CORN; SILICON DIOXIDE; STEARIC ACID; TITANIUM DIOXIDE

Defensol D

Active ingredients (in each tablet)

Acetaminophen 325 mg

Chlorpherinamine maleate 2 mg

Phenylephrine HCI 5 mg

Purpose

Pain Reliever/ Fever Reducer

Antihistamine

Nasal Decongestant

Uses

Temporarily relieves these symptoms associated with cold or flu:

- headache
- nasalcongestion
- sore throat
- fever
- minor aches and pains

Temporarily relieves minor aches, pains and headache as well as these sympotoms of hay fever or other upper respiratory allergies:

- runny nose
- sneezing
- nasal congestion
- itching of the nose or throat
- itchy, watery eyes

Temporarily relieves minor aches, pains, headache and nasal congestion as well as sinus congestion and pressure, and reduces swelling of nasal passages

Warnings

Liver Warning:This product contains acetaminophen. Severe liver damage may occur if you take

- more than 8 tablets in any 24-hour period, which is the maximum daily amount
- with other drugs containing acetaminophen
- 3 or more alcoholic drinks every day while using this product

Sore throat warning:if sore throat is severe, persits for more than 2 days, is accompanied or followed by fever, headache, rash, nausea, or vomiting, consult a doctor promptly.

Do not use

- To sedate a child or to make a child sleepy
- if you are now taking a prescription monoamine oxidase inhibitor (MAOI) (certain drugs for depression, psychiatric, or emotional conditions, or Parkinson's disease), or for two weeks after stopping the MAOI, drug. If you do not know if your prescription drug contains an MAOI, ask a doctor or pharmacist before taking this product.
- with any other drug containing acetaminophen (prescription or non prescription). If you are not sure whether a drug contains acetaminophen, ask a doctor or pharmacist.

Ask doctor before use if you have

- liver desease
- heart disease
- high blood pressure
- thyroid disease
- diabetes
- trouble urinating due to an enlarged prostate gland
- glaucoma
- a breathing problem such as emphysema, asthma, or chronic bronchitis

Ask a doctor or pharmacist before use if you are

- taking the blood thinning drug warfarin
- taking any other oral nasal decongestant or stimulant
- taking any other pain reliever/ fever reducer
- taking sedatives or tranquilizers

When using this product

- do not use more than directed
- excitability may occur with children
- drowsiness may occur
- avoid alcoholic beverages
- alcohol, sedatives and tranquilizers may increase drowsiness
- use caution when driving a motor vehicle or operating machinery

Stop use and ask a doctor if

- you get nervous, dizzy or sleepless
- pain or nasal congestion gets worse or lasts more than 7 days
- fever gets worse or lasts more than 3 days
- redness or swelling is present
- new symptoms occur

PREGNANCY OR BREAST FEEDING

If pregnant or breast-feeding,ask a health professional before use.

Keep out of reach of children.

OVERDOSAGE

Overdose warning:In case of overdose, get medical help or contact a Poison Control Center right away. Prompt medical attention is critical for adults as well as for children even if you do not notice any signs or symptoms.

DOSAGE AND ADMINISTRATION

Directions: do not take more than 8 tablets in a 24 hour period.

- do not exceed recommended dosage. Taking more than the recommended dose (overdose) may cause serious liver damage

age | dose
adults and children 12 years and over | 2 tablets every 4 hours
children under 12 years | do not use

INACTIVE INGREDIENT

Inactive ingredients:FD&C blue #2, hypromellose, magnesium stearate, PEG 400, povidone, pregelatinized starch, silicon dioxide, stearic acid, titanium dioxide

QUESTIONS

Questions?Menper Distributors, Inc. 1-800-560-5223;M-F 9 AM - 4 PM Eastern